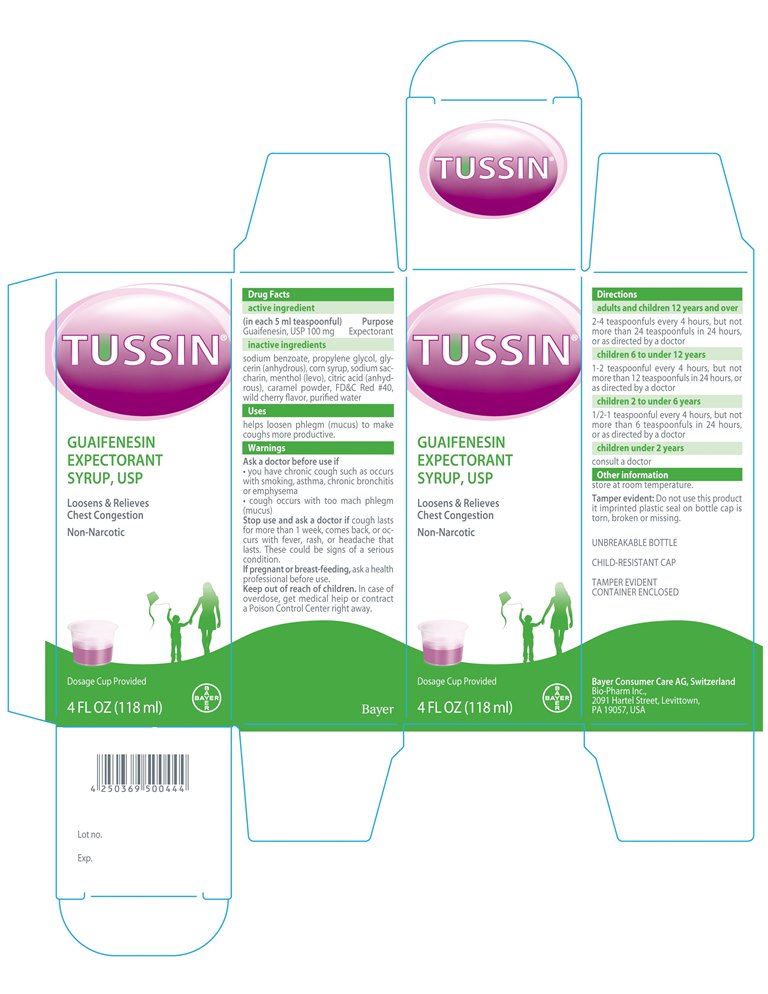 DRUG LABEL: Tussin
NDC: 61841-403 | Form: SYRUP
Manufacturer: Bayer HealthCare LLC
Category: otc | Type: HUMAN OTC DRUG LABEL
Date: 20150114

ACTIVE INGREDIENTS: GUAIFENESIN 100 mg/5 mL
INACTIVE INGREDIENTS: SODIUM BENZOATE; SACCHARIN SODIUM; MENTHOL, UNSPECIFIED FORM; PROPYLENE GLYCOL; GLYCERIN; CORN SYRUP; CITRIC ACID MONOHYDRATE; FD&C RED NO. 40; WATER

Tussin-Export Only

Active Ingredients (in each 5ml teaspoonful)

Guaifenesin, USP 100 mg

Purpose

Expectorant

INDICATIONS AND USAGE

Helps loosen phlegn (mucus) to make coughs more productive.

Ask a doctor before use if

- you have chronic cough such as occurs with smoking, asthma, chronic bronchitis or emphysema
- cough occurs with too much mach phlegm (mucus)

Stop use and ask a doctor if cough lasts for more than 1 week, comes back, or occurs with fever, rash, or headache that lasts. These could be signs of a seriuos conditions.

PREGNANCY OR BREAST FEEDING

If pregnant or breast-feeding, ask a health professional before use.

Keep out of reach of children. In case of overdose, get medical help or contact a Poison Control Center right away.